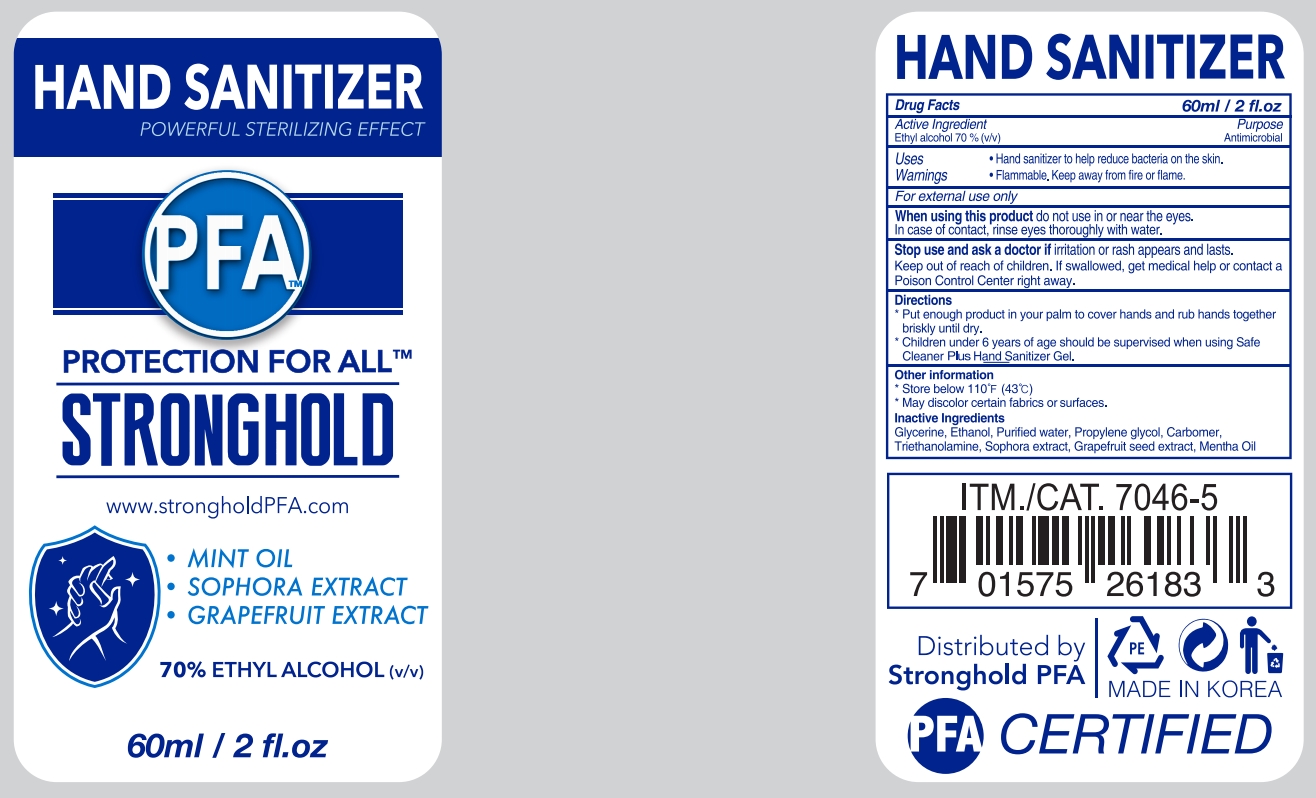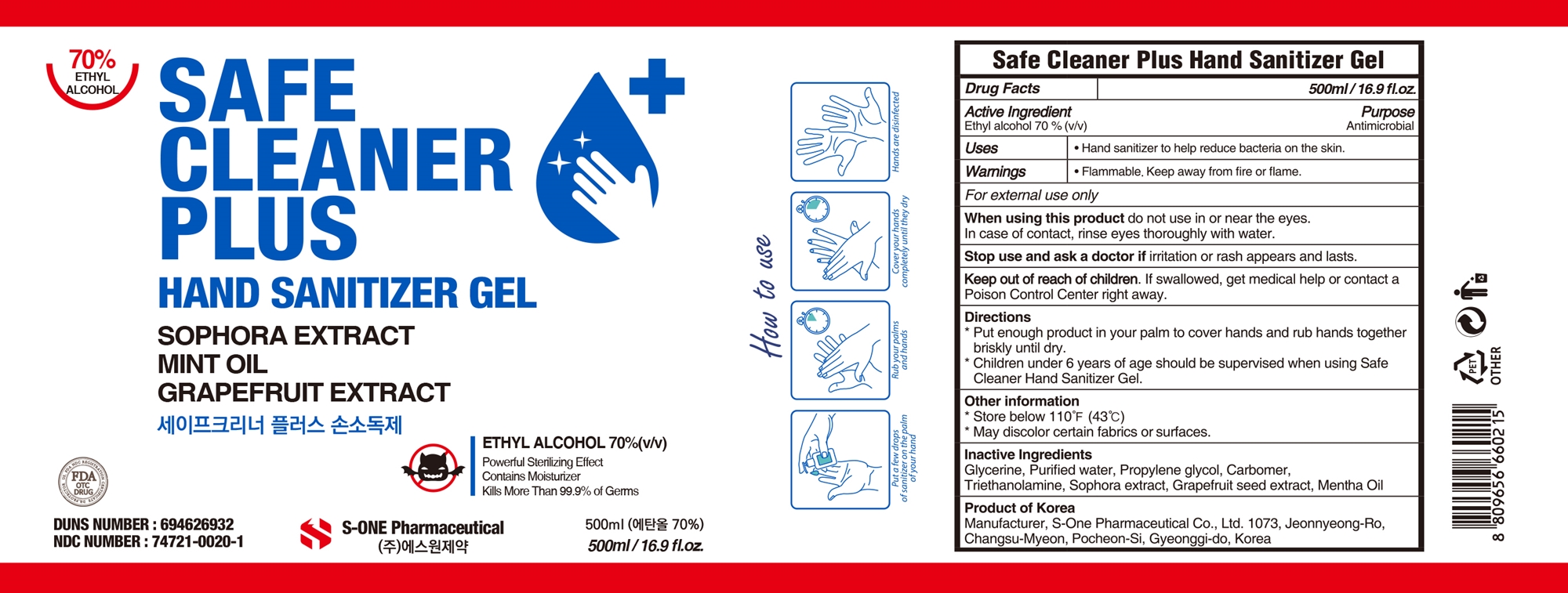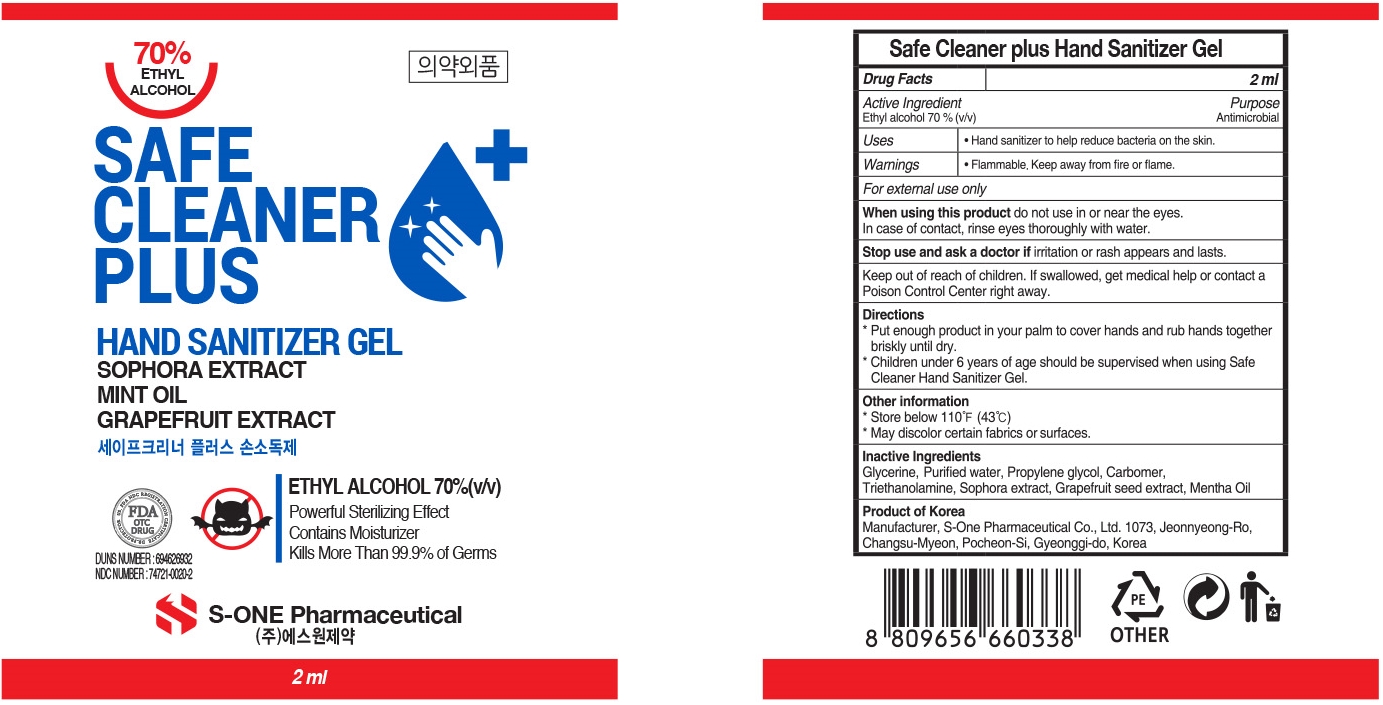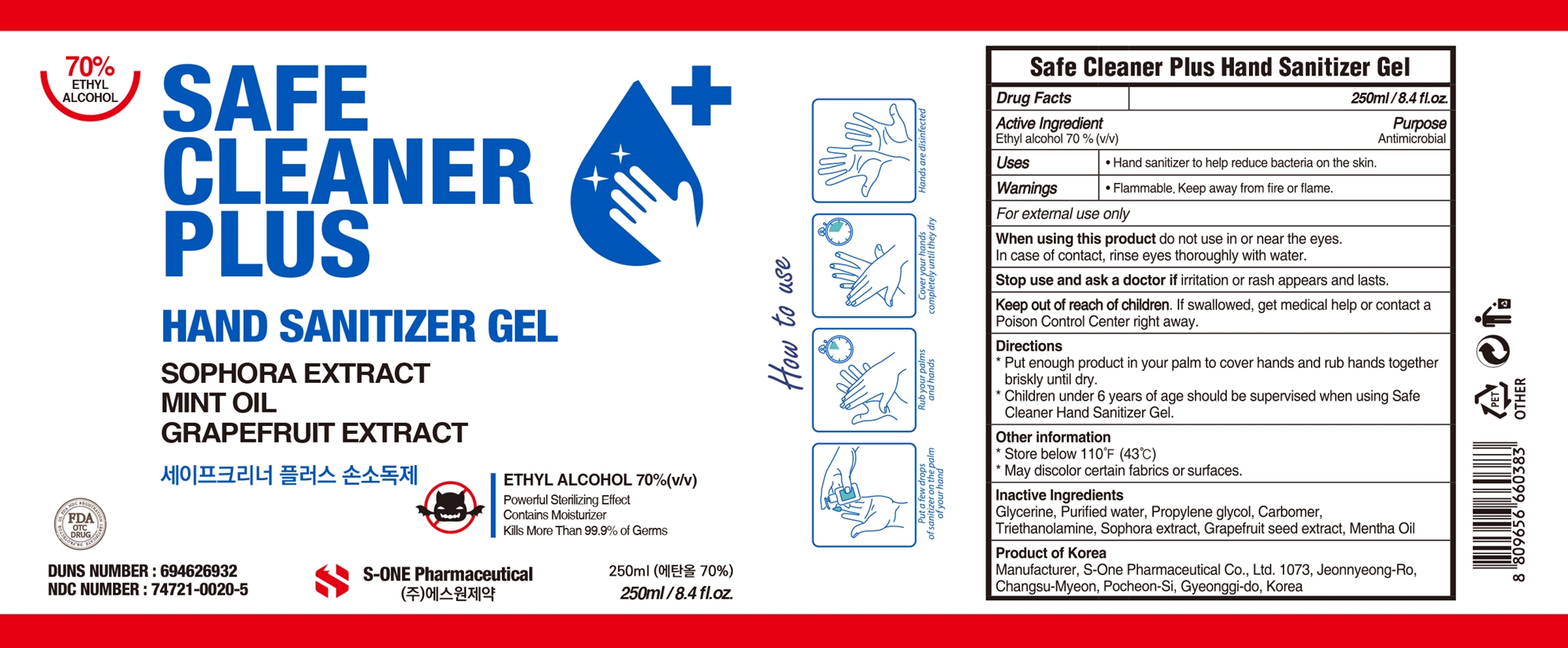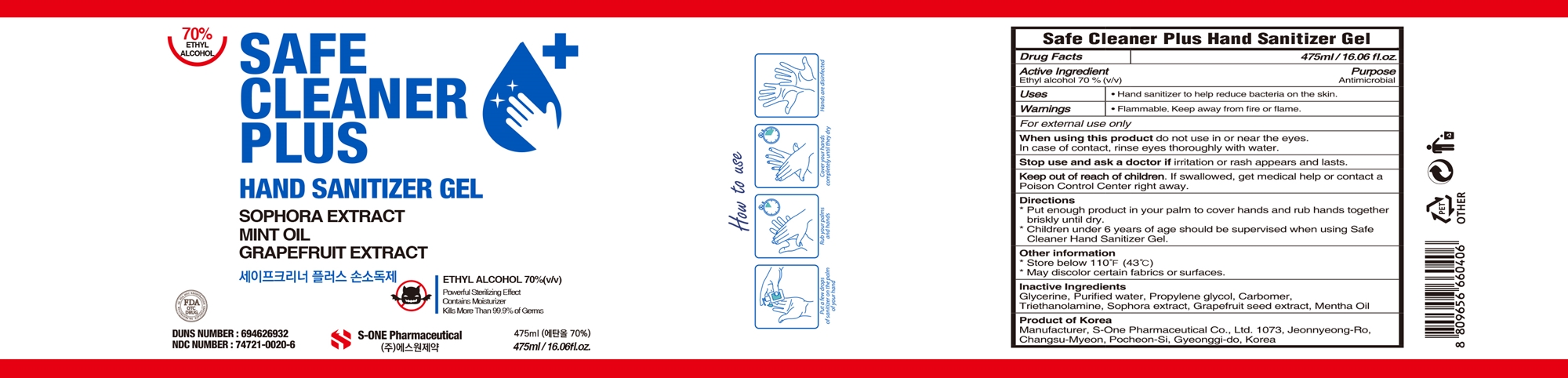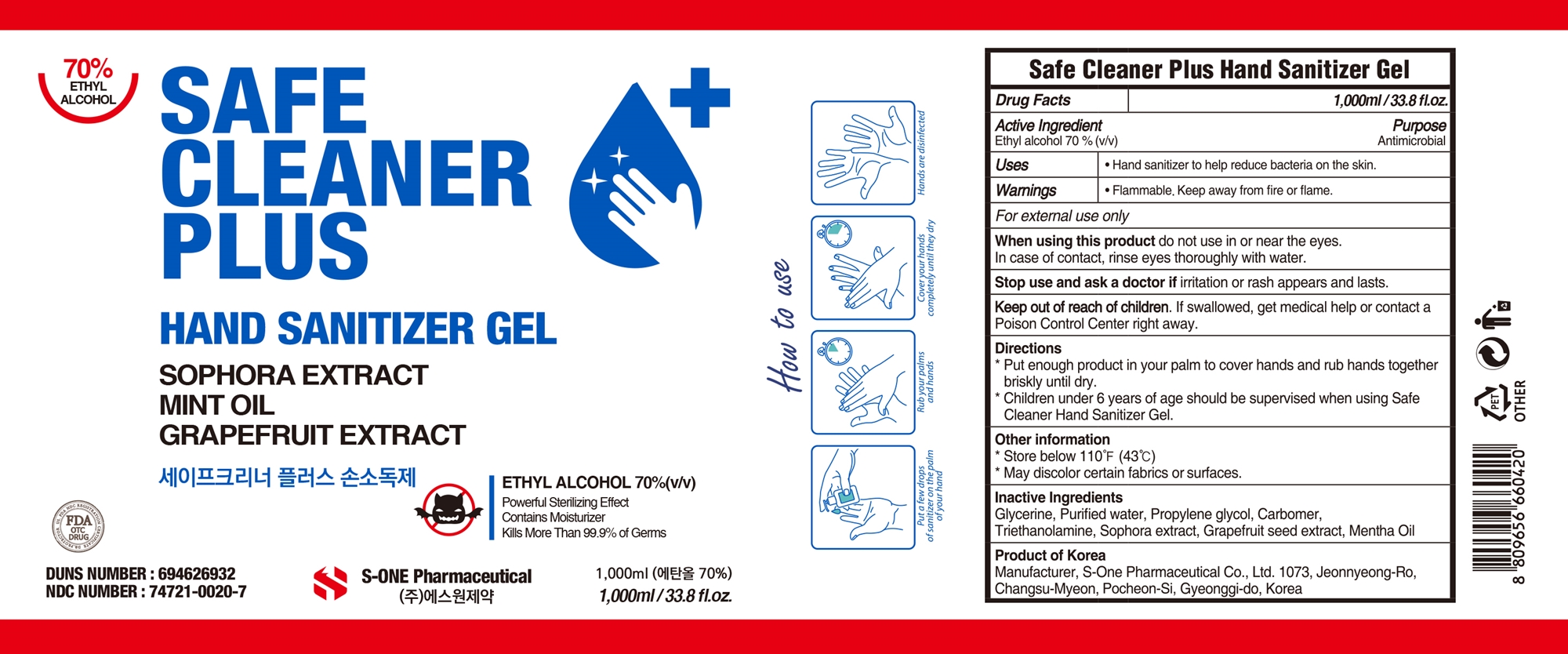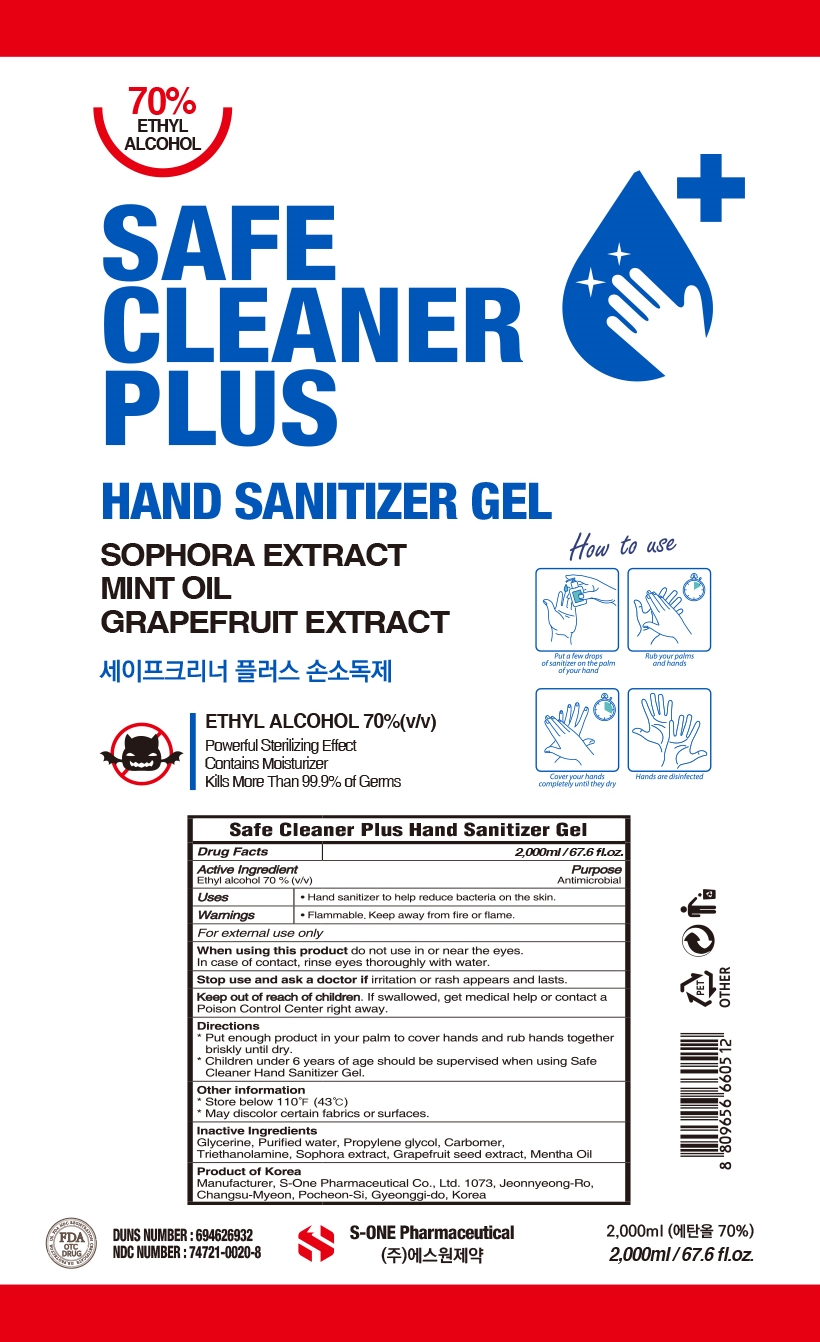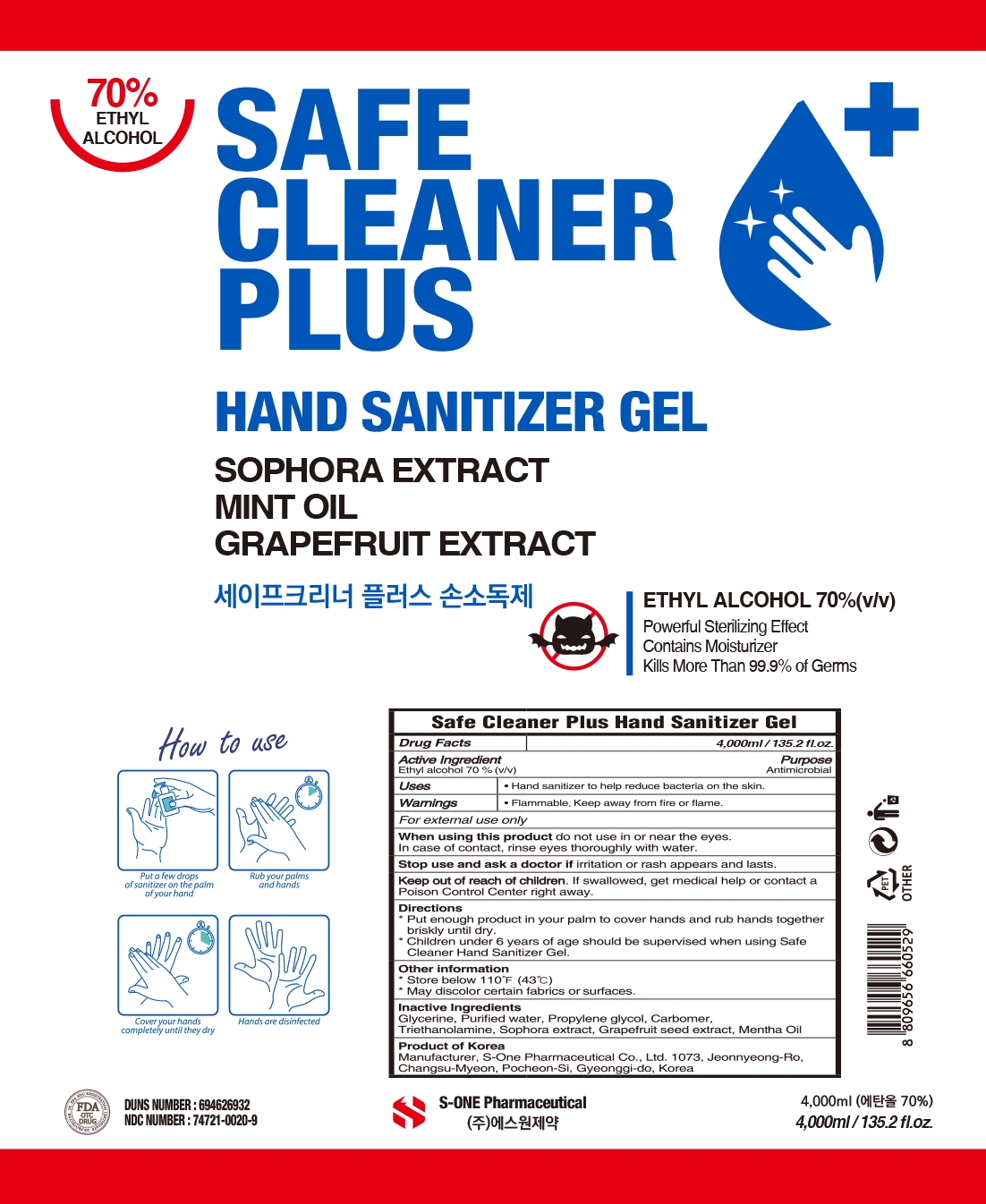 DRUG LABEL: SAFE CLEANER PLUS
NDC: 74721-0020 | Form: GEL
Manufacturer: S-ONE PHARMACEUTICAL INC
Category: otc | Type: HUMAN OTC DRUG LABEL
Date: 20200707

ACTIVE INGREDIENTS: ALCOHOL 70 mL/100 mL
INACTIVE INGREDIENTS: PROPYLENE GLYCOL; PEPPERMINT OIL; CARBOMER HOMOPOLYMER, UNSPECIFIED TYPE; GLYCERIN; WATER; TROLAMINE; SOPHORA FLAVESCENS ROOT; CITRUS PARADISI SEED

74721-0020

Active Ingredient

Ethyl alcohol 70%

Purpose

Antimicrobial

Uses

Hand sanitizer to help reduce bacteria on the skin.

Warnings

Flammable. Keep away from fire or flame.

For external use only

When using this product

do not use in or near the eyes.

In case of contact, rinse eyes thoroughly with water.

Stop use and ask a doctor if

irritation or rash appears and lasts.

Keep out of reach of children.

If swallowed, get medical help or contact a Poison Control Center right away.

Directions

* Put enough product in your palm to cover hands and rub hands together briskly until dry.

* Children under 6 years of age should be supervised when using Safe Cleaner Hand Sanitizer Gel.

Other information

* Store below 110F (43C)

* May discolor certain fabrics or surfaces.

Inactive Ingredients

Glycerine, Purified water, Propylene glycol, Carbomer, Triethanolamine, Sophora extract, Grapefruit seed extract, Mentha oil